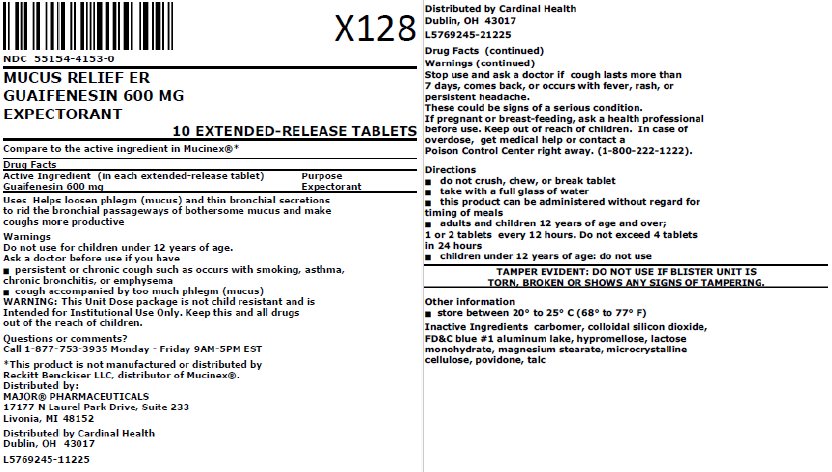 DRUG LABEL: Mucus Relief ER
NDC: 55154-4153 | Form: TABLET, EXTENDED RELEASE
Manufacturer: Cardinal Health 107, LLC
Category: otc | Type: HUMAN OTC DRUG LABEL
Date: 20251218

ACTIVE INGREDIENTS: GUAIFENESIN 600 mg/1 1
INACTIVE INGREDIENTS: CARBOMER HOMOPOLYMER TYPE B (ALLYL SUCROSE CROSSLINKED); SILICON DIOXIDE; FD&C BLUE NO. 1 ALUMINUM LAKE; HYPROMELLOSE, UNSPECIFIED; LACTOSE MONOHYDRATE; MAGNESIUM STEARATE; MICROCRYSTALLINE CELLULOSE; POVIDONE, UNSPECIFIED; TALC

Drug Facts

Active ingredient (in each extended-release tablet)

Guaifenesin 600 mg

Purpose

Expectorant

Uses

Helps loosen phlegm (mucus) and thin bronchial secretions to rid the bronchial passageways of bothersome mucus and makes coughs more productive.

Warnings

Do not use

for children under 12 years of age.

Ask a doctor before use if you have

- persistent or chronic cough such as occurs with smoking, asthma, chronic bronchitis or emphysema
- cough accompanied by too much phlegm (mucus)

Stop use and ask a doctor if

cough lasts more than 7 days, comes back, or occurs with fever, rash or persistent headache. These could be signs of a serious illness.

If pregnant or breast-feeding,

ask a health professional before use.

Keep out of reach of children.

In case of overdose, get medical help or contact a Poison Control Center right away (1-800-222-1222).

Directions

- do not crush, chew, or break tablet
- take with a full glass of water
- this product can be administered without regard for the timing of meals
- adults and children 12 years of age and over: 1 or 2 tablet every 12 hours. Do not exceed 4 tablets in 24 hours.
- children under 12 years of age: do not use

Other information

- store between 20º to 25ºC (68º to 77ºF)

Inactive ingredients

carbomer, colloidal silicon dioxide, FD&C blue #1 aluminum lake, hypromellose, lactose monohydrate, magnesium stearate, microcrystalline cellulose, povidone, talc

Questions or comments?

Call 1-877-753-3935 Monday-Friday 9AM-5PM EST

.

*This product is not manufactured or distributed by Reckitt Benckiser LLC, distributor of Mucinex®.

Distributed by:

MAJOR® PHARMACEUTICALS

Indianapolis, IN 46268

(800) 616-2471

www.major-rugby.com

Distributed By:

Cardinal Health

Dublin, OH 43017

L5769245-10225 / L5769245-20225

Product of India

Rev. 08/24 | M-58 | Re-order No. 701018

Principal Display Panel

NDC 55154-4153-0

MUCUS RELIEF ER

GUAIFENESIN 600 MG

EXPECTORANT

10 EXTENDED-RELEASE TABLETS